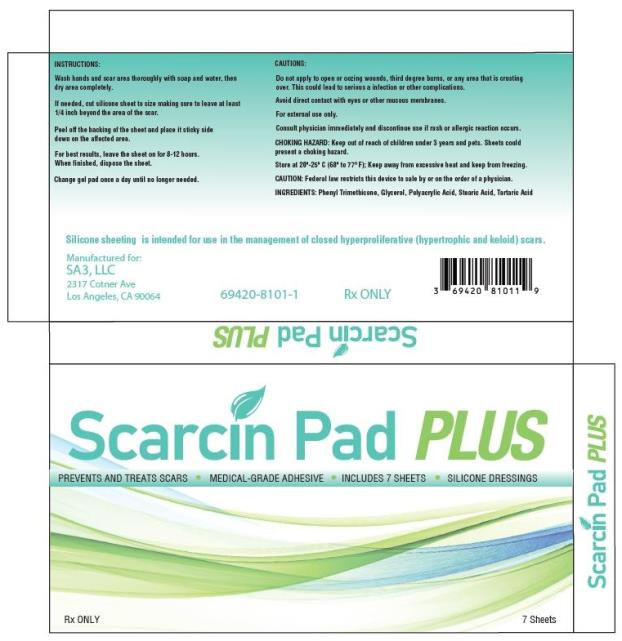 DRUG LABEL: Scarcin Pad PLUS
NDC: 71073-213 | Form: GEL
Manufacturer: Beijing HKKY Medical Tech. Co., Ltd.
Category: other | Type: MEDICAL DEVICE
Date: 20210905

71073-213_Scarcin Pad PLUS

Clinical Pharmacology

The exact mechanism of action in improving the appearance of scar tissue from using silicone remains unknown. However, various suggestions have been made to explain the efficacy of silicone sheets, including hydration, pressure, temperature, oxygen transmission and silicone absorption. There is some evidence that the treatment affects the stratum corneum and, by reducing evaporation, restores better homeostasis in the tissue. In keloid and hypertrophic scarring, the stratum corneum allows more evaporation of water from the underlying tissue than occurs in normal skin. Silicone pads may prevent this, keeping the stratum corneum in optimal hydration and protecting the skin from environmental hazards, both of which can reduce abnormal scarring. The gel may also affect the stratum corneum by inhibiting mast cell activity, diminishing edema, vasodilatation and excessive extracellular matrix formation but the simple changes in temperature, pressure, oxygen tension and hydration produced by wound coverage probably constitute the main mechanism of action. Another hypothesis is that the effect of static electricity on silicone may influence the alignment of collagen deposition.

INDICATIONS AND USES

For use in the management of closed hyperproliferative (hypertrophic or keloid) scars.

Contraindications

SCARCIN PAD PLUS is contraindicated in patients with known hypersensitivity to silicone or any of the listed ingredients.

Warnings

For external use only. Avoid contact with eyes, lips or mucous membranes. Do not apply on areas of broken skin. Do not apply on third degree burns and open wounds. Never use on sutured wound until sutures have been removed.

Precautions

Stop use and ask a doctor if irritation develops. In rare instances, silicone sheets may cause a rash on the skin. This condition may result from improper cleansing of the scar area where the silicone pad has been applied. If this product is applied properly and skin irritation still occurs, discontinue use and consult your physician. If ingested, get medical help or contact Poison Control Center right away.
KEEP THIS AND ALL MEDICATION OUT OF THE REACH OF CHILDREN.
This medication should be used as directed by your physician during pregnancy or while breastfeeding. Consult your doctor about the risks and benefits.

CAUTION: Federal law restricts this device to sale by or on the order of a physician.

Adverse Reactions

On rare occasions, the Pads may cause temporary redness, stinging, burning or irritation and normally disappear when the medication is discontinued.

Dosage and Administration

1. Wash hands and scar area thoroughly with soap and water. Completely dry the area after.
2. If needed, cut the SCARCIN PAD PLUS to size making sure to leave at least 1/4” beyond the area of the scar.
3. Peel off the backing of the sheet and place it sticky side down on the affected area.
4. For best results, leave on for 8-12 hours. When finished, dispose of sheet.
5. Change gel pad once a day until no longer needed.

How is SCARCIN PAD PLUS Supplied

SCARCIN PAD PLUS (Silicone Gel Matrix) is supplied in:
Seven (7) Large Non-Sterile Silicone Gel Pads – in 1 Carton
NDC: 69420-8101-1

Store at 20°-25°C (68° to 77°F); Keep away from heat and protect from freezing. [See USP Controlled Room Temperature.]

PRINCIPAL DISPLAY PANEL

SCARCIN PAD PLUS
7 Sheets
Rx Only